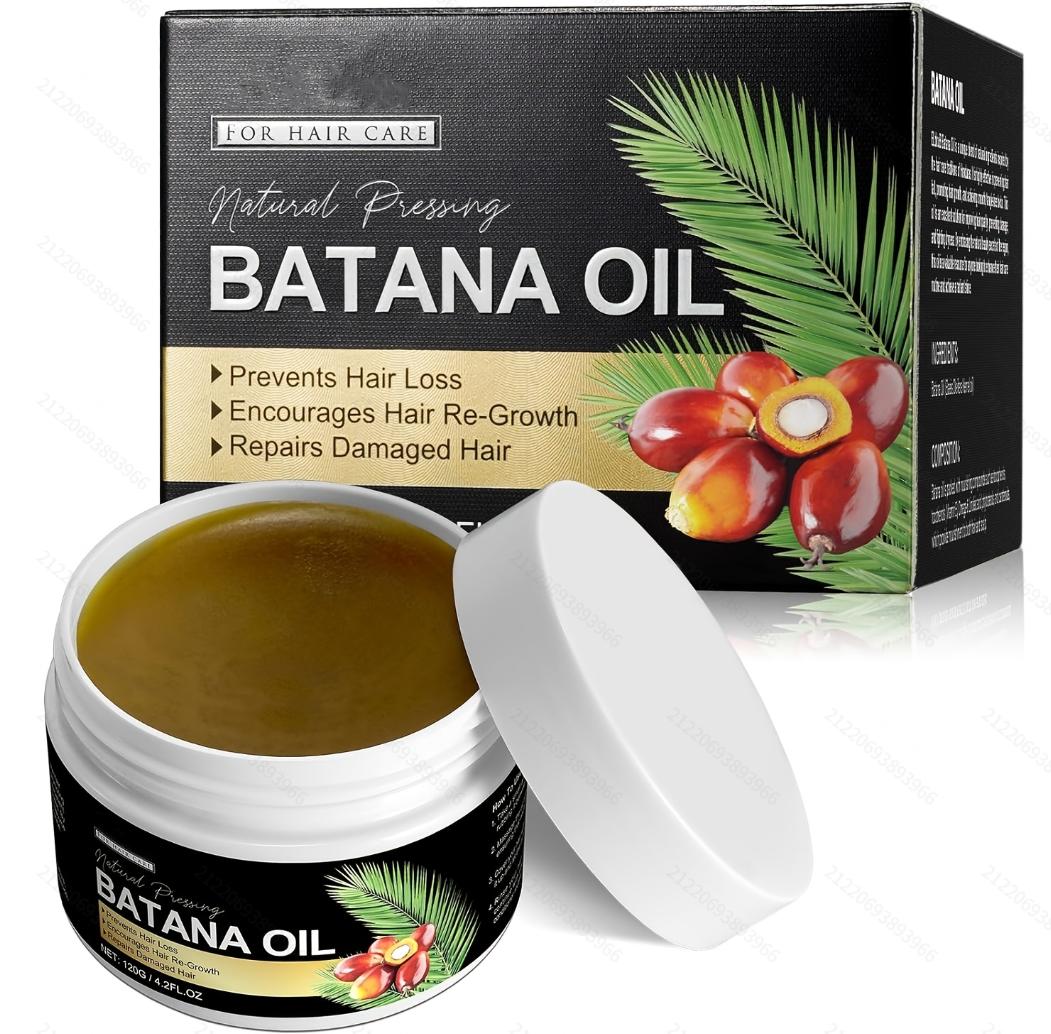 DRUG LABEL: SY1Batana Oil
NDC: 84778-033 | Form: CREAM
Manufacturer: Guangzhou Yixin Cross-border E-commerce Co., Ltd.
Category: otc | Type: HUMAN OTC DRUG LABEL
Date: 20241110

ACTIVE INGREDIENTS: DAVANA OIL 120 g/120 g
INACTIVE INGREDIENTS: WATER

COMPONENTS

Batana Oil 120g

PURPOSE

It nourishes and repairs hair, promotes hair growth, improves scalp health, moisturizes and repairs the skin

INDICATIONS AND USAGE

Pour an appropriate amount of Batana Oil into the palm of your hand and gently massage it onto your clean scalp, especially the hair roots. Leave the oil on your scalp for 20 to 30 minutes and then rinse.

WARNINGS

For external use only.
If sensitive irritation occurs, please stop using and store in a cool and dry place.

DO NOT USE

Please make sure your skin is clean before use.
Avoid using on open wounds or skin with allergic reactions.

WHEN USING

Take an appropriate amount of SY1 Batana Oil (usually about 2-3 drops) and pour it into the palm of your hand. Use your fingertips to gently massage the oil into your clean scalp, especially the roots of your hair. Massage your scalp for 5-10 minutes to ensure that the oil is fully penetrated. Wrap your hair with a towel or put on a shower cap and let the oil stay on your scalp for 20-30 minutes. You can even choose to use it at night and wash it off the next day.
Effect: It helps to promote blood circulation, nourish the scalp, and promote healthy hair growth.

Do not use on open wounds or allergic skin.

KEEP OUT OF REACH OF CHILDREN

If sxralowed, get medical help or contact a Poison Conirol Cenler ngiht away.

INACTIVE INGREDIENT

water